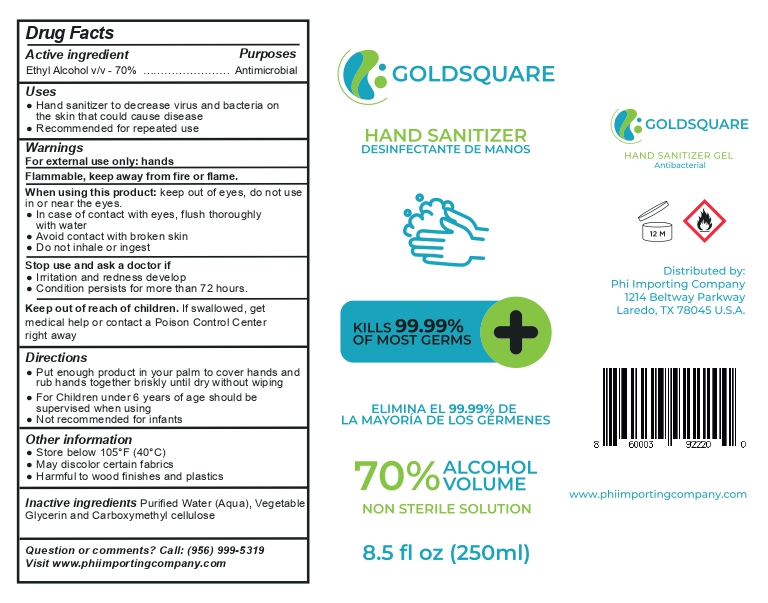 DRUG LABEL: HAND SANITIZER
NDC: 77210-0009 | Form: GEL
Manufacturer: EXPORTADORA IN & OUT S DE SR DE CV
Category: otc | Type: HUMAN OTC DRUG LABEL
Date: 20200613

ACTIVE INGREDIENTS: ALCOHOL 70 mL/100 mL
INACTIVE INGREDIENTS: WATER 21.8 mL/100 mL; CARBOXYMETHYLCELLULOSE 5 mL/100 mL; GLYCERIN 3.2 mL/100 mL

Active ingredient

Ethyl alcohol v/v 70%

purposes

antimicrobial

uses

hand sanitizer to decrease virus and bacteria on the skin that could cause disease

recommended for repeated use

warnings

for external use only: hands

flammable, keep away from fire and flame

when using this product

keep out of eyes, do not use in or near the eyes

in case of contact with eyes , flush thorougly with water

avoid contact with broken skin

do not inhale or ingest

when using this product

keep out of eyes, do not use in or near the eyes

in case of contact with eyes , flush thorougly with water

avoid contact with broken skin

do not inhale or ingest

stop use and ask a doctor if

irritation and redness develop

condition persist for more than 72 hours

keep out of reach of children

if swallowed, get medical help or contact poison control center right away

Directions

put enough product in your palm to cover hands and rub hands together briskly until dry without wiping

for children under 6 years of age shoul be supervised when using

not recommended for infants

other information

store below 105 F (40C)

may discolor certain fabrics

harmful to wood finishes and plastics

inactive ingredients

purified water (aqua), vegetable glycerin and carboxymethyl cellulose

principal display

hand sanitizer

desinfectante de manos

kills 99.9% de la mayoria de germenes

70% alcohol volume

non sterile solution

8.5 fl oz (250 ml)